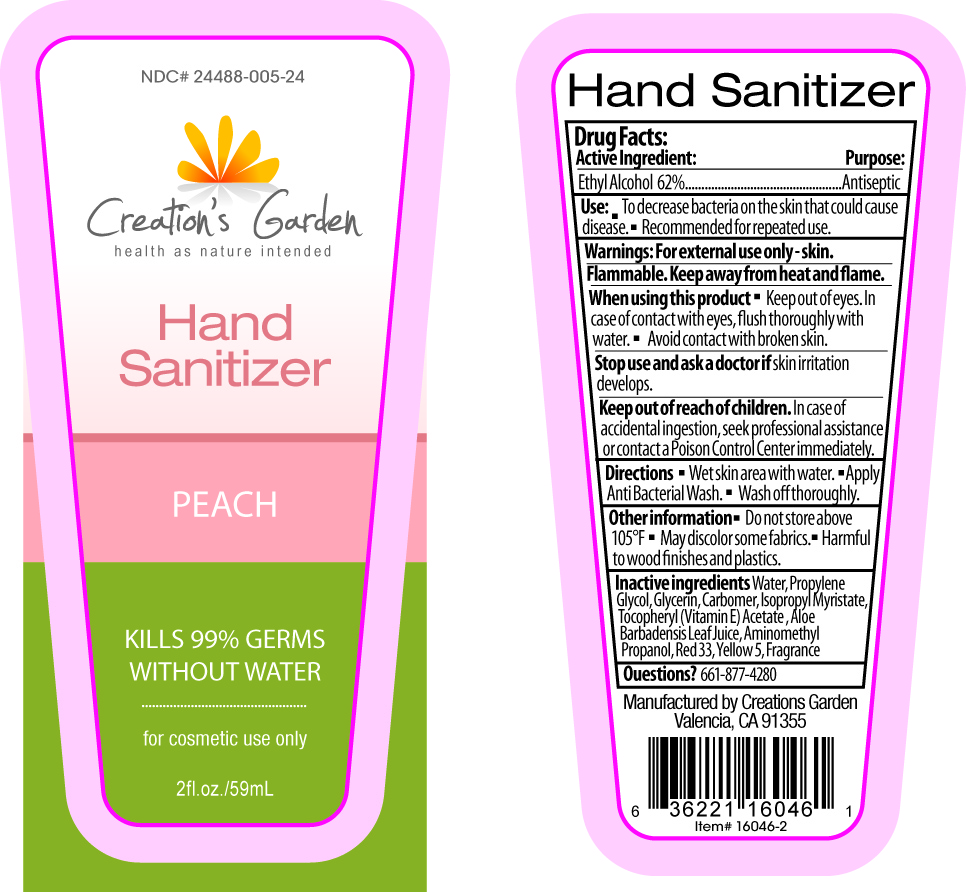 DRUG LABEL: Creations Garden
NDC: 24488-005 | Form: GEL
Manufacturer: Creation's Garden Natural Products, Inc
Category: otc | Type: HUMAN OTC DRUG LABEL
Date: 20100423

ACTIVE INGREDIENTS: ALCOHOL 36.58 mL/59 mL
INACTIVE INGREDIENTS: Water; PROPYLENE GLYCOL; GLYCERIN; ISOPROPYL MYRISTATE; ALPHA-TOCOPHEROL ACETATE; ALOE VERA LEAF; AMINOMETHYLPROPANOL; FD&C YELLOW NO. 5; D&C RED NO. 33; CARBOMER HOMOPOLYMER TYPE C; PEACH

Drug Facts

ACTIVE INGREDIENT

Ethyl Alcohol 62%

Purpose

.................................Antiseptic

Use

- To decrease bacteria on the skin that could cause disease.
- Recommended for repeated use.

Warnings

For external use only - skin.

Flammable. Keep away from heat and flame.

Keep out of reach of children.

In case of accidental ingestion, seek professional assistance or contact a Poison Control Center immediately

When using this product

- Keep out of eyes. In case of contact with eyes, flush thoroughly with water
- Avoid contact with broken skin

Stop use and ask a doctor if

- Stop use and ask doctor if skin irritation develops

Directions

- Wet skin area thoroughly with product.
- Rub hands together until dry

Other information

Do not store above 105° May discolor some fabrics. Harmful to wood finishes and plastics.

Inactive Ingredients

Water, Propylene Glycol, Glycerin, Carbomer, Isopropyl Myristate, Tocopheryl (Vitamin E) Acetate, Aloe Barbadensis Leaf Juice, Aminomethyl Propanol, Yellow 5, Red 33, Fragrance

Questions?

661-877-4280

PACKAGE LABEL

Placeholder Text